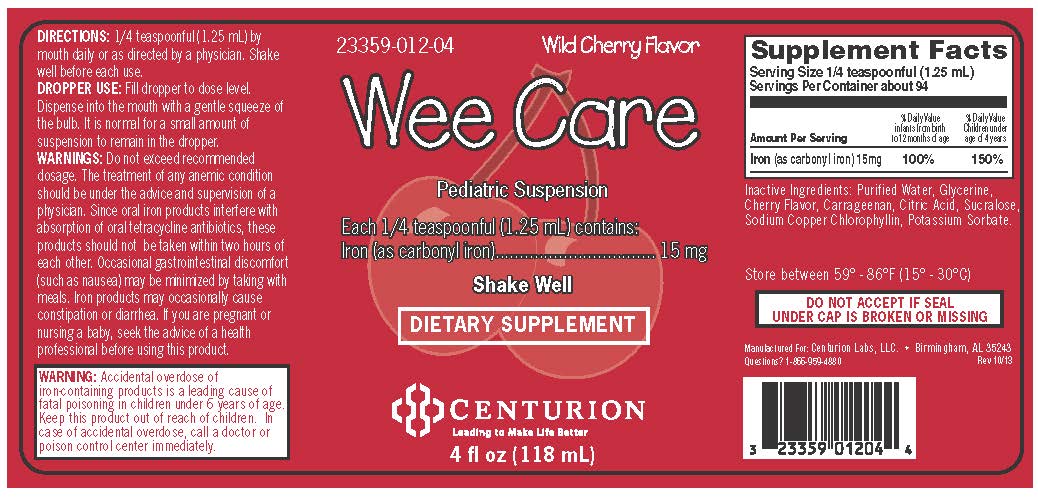 DRUG LABEL: Wee Care 
NDC: 23359-012 | Form: SUSPENSION
Manufacturer: Centurion Labs, LLC
Category: other | Type: DIETARY SUPPLEMENT
Date: 20141003

ACTIVE INGREDIENTS: Iron 15 mg/1.25 mL
INACTIVE INGREDIENTS: Water; Glycerin; Carrageenan; Citric Acid Monohydrate; Sucralose; Sodium Copper Chlorophyllin; Potassium Sorbate

STATEMENT OF IDENTITY SECTION

23359-012-04 Wild Cherry Flavor
Wee Care
Pediatric Suspension
Iron (as carbonyl iron)....... 15 mg
Purified Water, Glycerine, Cherry Flavor, Carrageenen, Citric Acid, Sucralose, Sodium Copper Chlorophyllin, Potassium Sorbate.

HEALTH CLAIM SECTION

Treatment of anemic condition

DOSAGE & ADMINISTRATION SECTION

1/4 teaspoonful (1.25 mL) by mouth daily or as directed by a physician. Shake well before each use.

DROPPER USE:
Fill dropper to dose level. Dispense into the mouth with a gentle squeeze of the bulb. It is normal for a small amount of suspension to remain in the dropper.

WARNINGS SECTION

Accidental overdose of iron-containing products is a leading cause of fatal poisoning in children under 6 years of age. Keep this product out of reach of children. In case of accidental overdose, call a doctor or poison control center immediately.

PRECAUTIONS SECTION

Do not exceed recommended dosage. The treatment of any anemic condition should be under the advice and supervision of a physician. Since oral iron products interfere with absorption of oral tetracycline antibiotics, these products should not be taken within two hours of each other. Occasional gastrointestinal discomfort (such as nausea) may be minimized by taking with meals. Iron products may occasionally cause constipation or diarrhea. If you are pregnant or nursing a baby, seek the advice of a health professional before using this product.

SAFE HANDLING WARNING SECTION

Store between 59° - 86°F (15° - 30°C)

PACKAGE LABEL.PRINCIPAL DISPLAY PANEL

23359-012-04 Wild Cherry Flavor
Wee Care
Pediatric Suspension
Each 1/4 teaspoonful (1.25 mL) contains: Iron (as carbonyl iron)................................. 15 mg
Shake Well
DIETARY SUPPLEMENT
CENTURION
Leading to Make Life Better
4 fl oz (118 mL)
Supplement Facts
Serving Size 1/4 teaspoonful (1.25 mL)
Servings Per Container about 94

Amount Per Serving | % Daily Value infants from birth to 12 months of age | % Daily Value Children under age of 4 years
Iron (as carbonyl iron) 15mg | 100% | 150%

DO NOT ACCEPT IF SEAL UNDER CAP IS BROKEN OR MISSING
Manufactured For: Centurion Labs, LLC. • Birmingham, AL 35243
Questions? 1-866-959-4880 Rev 10/13